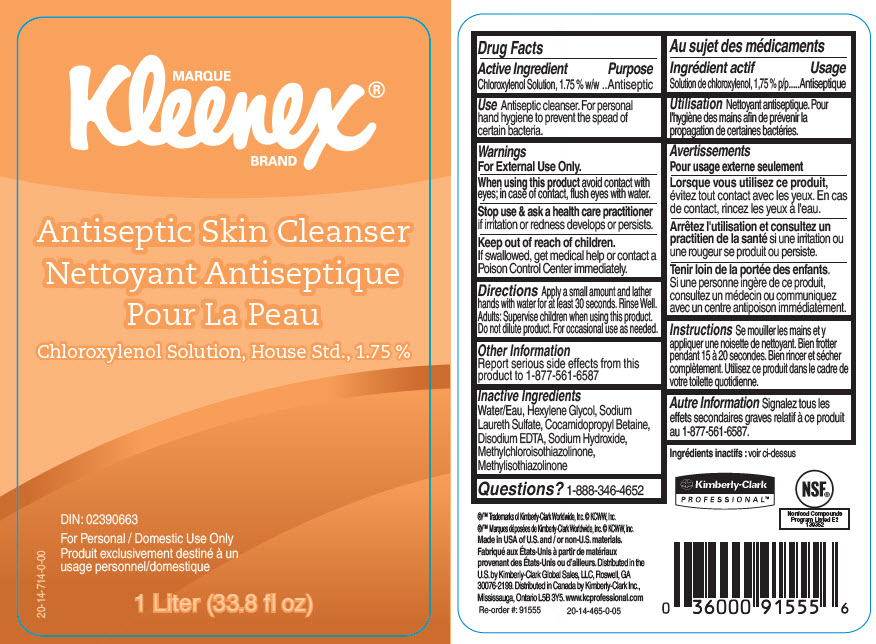 DRUG LABEL: Kleenex Antiseptic Skin Cleanser
NDC: 55118-571 | Form: SOLUTION
Manufacturer: Kimberly-Clark
Category: otc | Type: HUMAN OTC DRUG LABEL
Date: 20191016

ACTIVE INGREDIENTS: Chloroxylenol 17.5 g/1 L
INACTIVE INGREDIENTS: Water; Hexylene Glycol; Sodium Laureth-3 Sulfate; Cocamidopropyl Betaine; Edetate Disodium; Sodium Hydroxide; Methylchloroisothiazolinone; Methylisothiazolinone

Kleenex® Antiseptic Skin Cleanser

Drug Facts

Active Ingredient

Chloroxylenol Solution, 1.75 % w/w

Purpose

Antiseptic

Use

Antiseptic cleanser. For personal hand hygiene to prevent the spead of certain bacteria.

Warnings

For External Use Only.

When using this product avoid contact with eyes; in case of contact, flush eyes with water.

Stop use & ask a health care practitioner if irritation or redness develops or persists.

Keep out of reach of children.

If swallowed, get medical help or contact a Poison Control Center immediately.

Directions

Apply a small amount and lather hands with water for at least 30 seconds. Rinse Well.

Adults

Supervise children when using this product. Do not dilute product. For occasional use as needed.

Other Information

Report serious side effects from this product to 1-877-561-6587

Inactive Ingredients

Water/Eau, Hexylene Glycol, Sodium Laureth Sulfate, Cocamidopropyl Betaine, Disodium EDTA, Sodium Hydroxide, Methylchloroisothiazolinone, Methylisothiazolinone

Questions?

1-888-346-4652

Distributed in the
U.S. by Kimberly-Clark Global Sales, LLC, Roswell, GA
30076-2199. Distributed in Canada by Kimberly-Clark Inc.,
Mississauga, Ontario L5B 3Y5.

PRINCIPAL DISPLAY PANEL - 1 Liter Container Label

MARQUE
Kleenex®
BRAND

Antiseptic Skin Cleanser

Chloroxylenol Solution, House Std., 1.75 %

DIN: 02390663

For Personal / Domestic Use Only

1 Liter (33.8 fl oz)

20-14-714-0-00